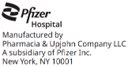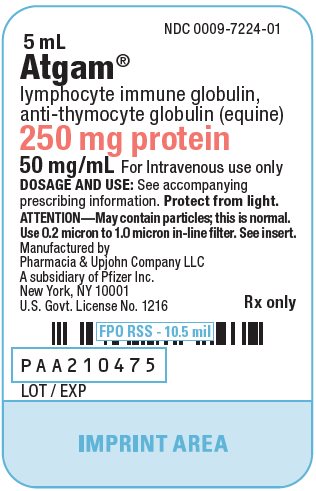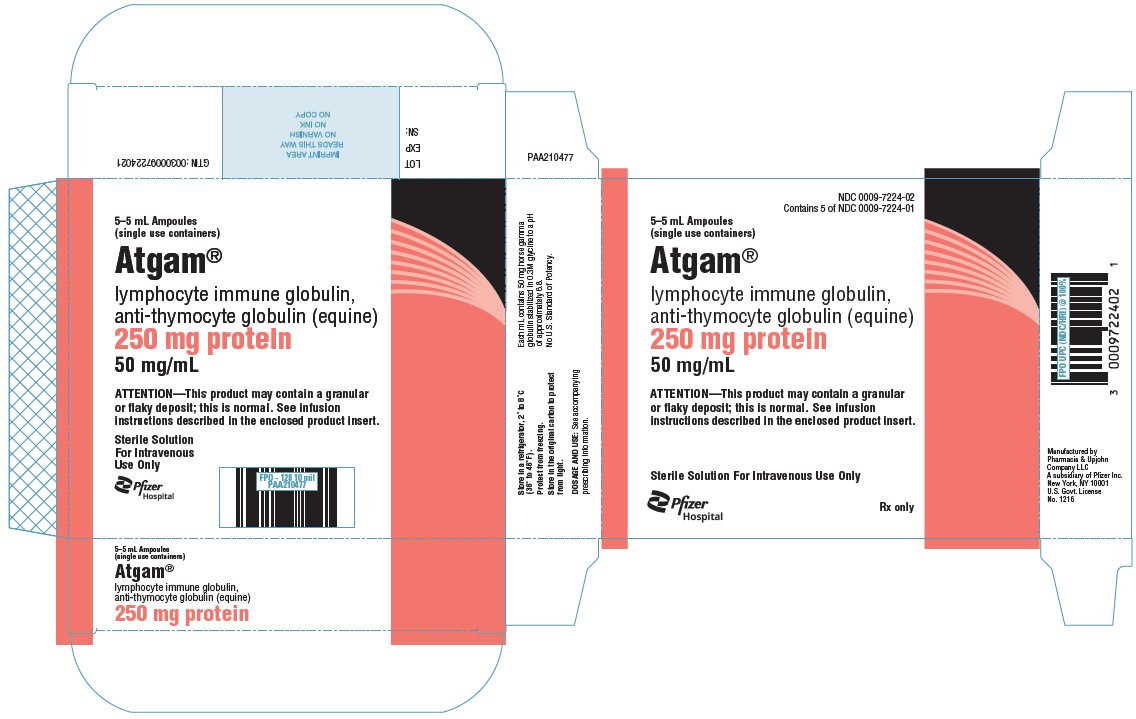 DRUG LABEL: Atgam
NDC: 0009-7224 | Form: INJECTION, SOLUTION
Manufacturer: Pharmacia & Upjohn Company LLC
Category: other | Type: PLASMA DERIVATIVE
Date: 20240618

ACTIVE INGREDIENTS: EQUINE THYMOCYTE IMMUNE GLOBULIN 50 mg/1 mL
INACTIVE INGREDIENTS: GLYCINE

HIGHLIGHTS OF PRESCRIBING INFORMATION

These highlights do not include all the information needed to use ATGAM safely and effectively. See full prescribing information for ATGAM.
ATGAM® (lymphocyte immune globulin, anti-thymocyte globulin [equine]), sterile solution, for intravenous use only
Initial U.S. Approval: 1981

RECENT MAJOR CHANGES

Boxed Warning | 5/2023
Dosage and Administration (2) | 5/2023
Contraindications (4) | 5/2023
Warnings and Precautions (5) | 5/2023

WARNING: ANAPHYLAXIS

See full prescribing information for complete boxed warning.

Anaphylaxis has been reported with the use of ATGAM. ATGAM can cause potentially life‑threatening anaphylaxis when injected intravenously. Monitor patients for signs and symptoms of anaphylaxis during infusion and for at least 24 hours after infusion [see Warnings and Precautions (5.1) and Adverse Reactions (6.1)].

1 INDICATIONS AND USAGE

ATGAM is an immunoglobulin G indicated for:

- Renal allograft rejection. (1.1)
- Aplastic anemia (moderate to severe) in patients unsuitable for bone marrow transplantation. (1.2)
- Limitations of Use:
  The usefulness of ATGAM has not been demonstrated in patients with aplastic anemia who are suitable candidates for bone marrow transplantation or in patients with aplastic anemia secondary to neoplastic disease, storage disease, myelofibrosis, Fanconi's syndrome, or in patients known to have been exposed to myelotoxic agents or radiation. (1.2)

2 DOSAGE AND ADMINISTRATION

For intravenous use only.

Indication | Dosage
Renal allograft rejection | 10 to 15 mg/kg daily intravenously for 14 days; additional alternate-day therapy up to a total of 21 doses may be given. (2.1)
Aplastic anemia | 10 to 20 mg/kg daily intravenously for 8 to 14 days; additional alternate-day therapy up to a total of 21 doses may be given. (2.1)

3 DOSAGE FORMS AND STRENGTHS

ATGAM 50 mg/mL concentrate for solution for infusion. (3)

4 CONTRAINDICATIONS

Anaphylactic reaction during prior administration of ATGAM or any other equine gamma globulin preparation. (4)

5 WARNINGS AND PRECAUTIONS

- Anaphylaxis, which can be life-threatening, has been reported. To identify those at greatest risk, skin testing before treatment is strongly recommended. Discontinue ATGAM if anaphylaxis occurs. (5.1)
- Monitor patients for signs and symptoms of cytokine release syndrome. (5.2)
- Monitor patients for signs and symptoms of infusion-associated reactions. (5.3)
- Monitor patients for signs and symptoms of serum sickness. (5.4)
- Monitor and report any infection suspected to have been transmitted. (5.5)
- Monitor patients for concurrent infection, including cytomegalovirus, Epstein-Barr virus, and herpes simplex virus infection. (5.6)
- Do not administer live vaccines to patients about to receive, receiving, or after treatment with ATGAM due to a potential of uncontrolled viral replication in the immunosuppressed patient. (5.7)
- Consider discontinuing therapy if severe and unremitting thrombocytopenia or neutropenia occurs. (5.8)
- Monitor liver and renal function as clinically indicated and manage according to relevant clinical guidelines. (5.9)

6 ADVERSE REACTIONS

The most common (incidence >10%) adverse reactions are pyrexia, chills, rash, thrombocytopenia, leukopenia, and arthralgia. (6.1)
To report SUSPECTED ADVERSE REACTIONS, contact Pfizer Inc. at 1-800-438-1985 or FDA at 1-800-FDA-1088 or www.fda.gov/medwatch.

7 DRUG INTERACTIONS

Previously masked reactions to ATGAM may appear following reduced doses of immunosuppressants. (7)

8 USE IN SPECIFIC POPULATIONS

- Pregnancy: Use only if the potential benefit justifies the risk. (8.1)
- Lactation: Discontinue breast-feeding during treatment with ATGAM or discontinue ATGAM treatment. (8.2)
- Contraception: Advise females of reproductive potential to use effective contraception during treatment with ATGAM and for up to 10 weeks after cessation of therapy. Advise males with a female partner of reproductive potential to use effective contraception during treatment with ATGAM and for at least 10 weeks after cessation of therapy. (8.3)
- Geriatric: Start dosing at the low end of the dosage range. (8.5)

FULL PRESCRIBING INFORMATION

WARNING: ANAPHYLAXIS

Anaphylaxis has been reported with the use of ATGAM. ATGAM can cause potentially life‑threatening anaphylaxis when injected intravenously. Monitor patients for signs and symptoms of anaphylaxis during infusion and for at least 24 hours after infusion [see Warnings and Precautions (5.1) and Adverse Reactions (6.1)].

1 INDICATIONS AND USAGE

1.1 Renal Allograft Rejection

ATGAM is indicated for the management of allograft rejection in renal transplant patients; when administered with conventional therapy at the time of rejection ATGAM increases the frequency of resolution of the acute rejection episode [see Clinical Studies (14.1)].

1.2 Aplastic Anemia

ATGAM is indicated for the treatment of moderate to severe aplastic anemia in patients unsuitable for bone marrow transplantation [see Clinical Studies (14.2)].

The usefulness of ATGAM has not been demonstrated in patients with aplastic anemia who are suitable candidates for bone marrow transplantation or in patients with aplastic anemia secondary to neoplastic disease, storage disease, myelofibrosis, Fanconi's syndrome, or in patients known to have been exposed to myelotoxic agents or radiation.

2 DOSAGE AND ADMINISTRATION

For intravenous use only.

Administer ATGAM intravenously and use with concomitant immunosuppressants.

2.1 Dosing Information

Renal Allograft Rejection

The recommended dose is 10 to 15 mg/kg daily intravenously for 14 days. Additional alternate-day therapy up to a total of 21 doses may be given.

Aplastic Anemia (Moderate to Severe)

The recommended dose is 10 to 20 mg/kg daily intravenously for 8 to 14 days. Additional alternate-day therapy up to a total of 21 doses may be given.

2.2 Preparation and Administration Instructions

Preparation of Solution

- Visually inspect parenteral drug products for particulate matter and discoloration prior to administration, whenever solution and container permit. However, because ATGAM is a gamma globulin product, it can be transparent to slightly opalescent, colorless to faintly pink or faintly brown, and may develop a slight granular or flaky deposit. Do not shake ATGAM (diluted or undiluted) because excessive foaming and/or denaturation of the protein may occur.
- Dilute ATGAM for intravenous infusion in an inverted bottle/bag of sterile vehicle so the undiluted ATGAM does not contact the air inside. Add the total daily dose of ATGAM to the sterile vehicle (See Compatibility and Stability). Do not exceed a concentration of 4 mg of ATGAM per mL. Gently rotate or swirl the diluted solution to effect thorough mixing.

Administration

Diluted ATGAM should be at room temperature before infusion. ATGAM is appropriately administered into a vascular shunt, arterial venous fistula, or a high-flow central vein using an in-line filter (not supplied) with a pore size of 0.2 to 1.0 micron. Use the in-line filter (not supplied) with all infusions of ATGAM to prevent the administration of any insoluble material that may develop in the product. Use high-flow veins to minimize the occurrence of phlebitis and thrombosis. Infuse ATGAM over a period of at least 4 hours. Monitor patients for signs and symptoms of anaphylaxis during infusion and for at least 24 hours after infusion [see Warnings and Precautions (5.1) and Adverse Reactions (6)].

Compatibility and Stability

- Once diluted, ATGAM has been shown to be physically and chemically stable for up to 24 hours at concentrations of up to 4 mg per mL in the following diluents: 0.9% Sodium Chloride Injection, 5% Dextrose and 0.225% Sodium Chloride Injection, and 5% Dextrose and 0.45% Sodium Chloride Injection.
- Do not dilute ATGAM in Dextrose Injection, USP, as low salt concentrations may cause precipitation. Do not use highly acidic infusion solutions since these solutions may contribute to physical instability over time.
- Store diluted ATGAM at room temperature. The diluted solution must be infused within 24 hours (including infusion time).

3 DOSAGE FORMS AND STRENGTHS

ATGAM 50 mg/mL concentrate for solution for infusion

4 CONTRAINDICATIONS

Do not administer ATGAM to a patient who has had an anaphylactic reaction during prior administration of ATGAM or any other equine gamma globulin preparation [see Warnings and Precautions (5.1)].

5 WARNINGS AND PRECAUTIONS

5.1 Anaphylaxis

Anaphylaxis has been reported with the use of ATGAM. Anaphylaxis is potentially life-threatening. Discontinue ATGAM if anaphylaxis occurs. Generalized rash, tachycardia, dyspnea, and hypotension can be signs of an anaphylactic reaction.

Skin Testing

To identify those at greatest risk of systemic anaphylaxis, skin testing potential recipients is strongly recommended before commencing treatment. Consult an allergist for epicutaneous (prick) and intradermal testing and interpretation. Positive skin testing to ATGAM suggests clinical hypersensitivity and increased risk of a systemic allergic reaction (including anaphylaxis) should the drug be dosed intravenously. In the event of a positive skin test, seriously consider alternative forms of therapy. The predictive value of this test has not been proven clinically, and allergic reactions such as anaphylaxis have occurred in patients whose skin tests were negative. It is important to note that skin testing does not inform risk of delayed hypersensitivity reactions such as serum sickness.

Monitoring and Management of Anaphylaxis

Administer ATGAM in a healthcare facility where a physician familiar with the treatment of potentially life-threatening allergic reactions is in attendance. Monitor patients for signs and symptoms of anaphylaxis during infusion and for at least 24 hours after infusion of ATGAM. Have epinephrine and emergency equipment available for treatment of acute allergic symptoms, should they occur.

5.2 Cytokine Release Syndrome

Cytokine release syndrome has been reported with the use of ATGAM. Cytokine release syndrome can be fatal. Clinical signs may include fever, chills, headache, chest pain, hypotension, dyspnea, tachypnea, and edema. Monitor patients for signs and symptoms of cytokine release syndrome and manage according to relevant clinical guidelines.

5.3 Infusion-Associated Reactions

Serious infusion-associated reactions have been reported with the use of ATGAM. Clinical signs associated with infusion-associated reactions include generalized rash, tachycardia, dyspnea, and hypotension. Monitor patients for signs and symptoms of infusion-associated reactions and manage according to relevant clinical guidelines.

5.4 Serum Sickness

Serum sickness is a delayed hypersensitivity/immune reaction. Symptoms of serum sickness including rash, arthralgia, pyrexia, chills, and pain have been reported. Monitor patients for signs and symptoms of serum sickness and manage according to relevant clinical guidelines.

5.5 Transmissible Infectious Agents

Because ATGAM is made from equine and human blood components, it may carry a risk of transmitting infectious agents, e.g., viruses and the Creutzfeldt-Jakob disease (CJD) agent. This also applies to unknown or emerging viruses and other pathogens.

Report any infection suspected to have been transmitted by this product to Pfizer Inc. at 1-800-438-1985.

5.6 Infections

Due to the immunosuppressive effects of ATGAM, opportunistic infections (viral, bacterial and fungal) have been reported. Sepsis has also been reported. There is an increased risk of viral reactivation (e.g., cytomegalovirus [CMV], Epstein–Barr virus [EBV] infection, herpes simplex virus [HSV]). Monitor patients carefully for concurrent infection.

5.7 Immunizations

Do not administer live vaccines to patients about to receive, receiving, or after treatment with ATGAM. Concomitant administration of ATGAM with live virus vaccines carries a potential of uncontrolled viral replication in the immunosuppressed patient. There is insufficient information to fully define the extent of the risk, or the period of time during which the risk exists. If administered, live viruses may interfere with ATGAM treatment.

5.8 Thrombocytopenia and Neutropenia

Thrombocytopenia and neutropenia have been reported with the use of ATGAM. If thrombocytopenia occurs, consider platelet transfusions to maintain platelets at clinically acceptable levels. Consider discontinuing ATGAM if severe and unremitting thrombocytopenia or neutropenia occurs.

5.9 Hepatic and Renal Function Tests

In patients with aplastic anemia and other hematologic abnormalities who have received ATGAM, abnormal test results of liver function (SGOT, SGPT, alkaline phosphatase) and renal function (serum creatinine) have been observed. Monitor liver and renal functions as clinically indicated and manage according to relevant clinical guidelines.

6 ADVERSE REACTIONS

The most clinically significant adverse reactions are anaphylaxis, infection, thrombocytopenia, leukopenia, arthralgia, edema, bradycardia, and abnormal renal and liver function tests.

6.1 Clinical Trials Experience

Because clinical trials are conducted under widely varying conditions, adverse reaction rates observed in the clinical trials of a drug cannot be directly compared to rates in the clinical trials of another drug and may not reflect the rates observed in clinical practice.

The safety of ATGAM has been evaluated in 367 patients with renal allograft rejection and 109 patients with aplastic anemia.

The renal allograft rejection and aplastic anemia patients received a similar dosing regimen, and these data were pooled to obtain the frequencies listed in Tables 1 and 2 below.

The most commonly reported adverse reactions (occurring in greater than 10% of patients) are pyrexia, chills, rash, thrombocytopenia, leukopenia, and arthralgia.

Table 1. Adverse Reactions Occurring in ≥1% of Patients Who Received ATGAM
Adverse Reaction [Percentages are treatment-emergent all-causality events] , [Medical Dictionary for Regulatory Activities (MedDRA) Preferred Terms] | ATGAM
 | Frequency (%)
 | (N = 476)
Pyrexia | 39.5
Chills | 26.5
Rash | 25.6
Thrombocytopenia | 21.6
Leukopenia | 17.9
Arthralgia | 17.2
Urticaria | 9.2
Headache | 5.3
Pruritus | 4.6
Nausea | 4.2
Infection | 3.4
Vomiting | 3.4
Thrombophlebitis | 3.2
Hypertension | 2.9
Hypotension | 2.9
Diarrhea | 2.9
Abdominal pain upper | 2.7
Chest pain | 2.7
Infusion site pain | 2.1
Edema | 2.1
Bradycardia | 1.5
Back pain | 1.5
Lymphadenopathy | 1.3
Arteriovenous fistula thrombosis | 1.3
Dizziness | 1.1
Dyspnea | 1.1
Tachycardia | 1.1
Liver function test abnormal | 1.0

Table 2. Adverse Reactions Occurring in <1% of Patients Who Received ATGAM
Adverse Reaction [Percentages are treatment-emergent all-causality events] , [Medical Dictionary for Regulatory Activities (MedDRA) Preferred Terms] | ATGAM
 | Frequency (%)
 | (N = 476)
Convulsion | 0.8
Pleural effusion | 0.8
Night sweats | 0.8
Serum sickness | 0.6
Hyperglycemia | 0.6
Stomatitis | 0.6
Renal function test abnormal | 0.6
Herpes simplex | 0.4
Agitation | 0.4
Hiccups | 0.4
Proteinuria | 0.4
Asthenia | 0.4
Malaise | 0.4
Wound dehiscence | 0.4
Anaphylactic reaction | 0.2
Encephalitis | 0.2
Paresthesia | 0.2
Renal artery thrombosis | 0.2
Iliac vein occlusion | 0.2
Laryngospasm | 0.2
Pulmonary edema | 0.2
Dermatitis allergic | 0.2
Periorbital edema | 0.2
Toxic epidermal necrolysis | 0.2

6.2 Postmarketing Experience

The following adverse reactions have been identified during postapproval use of ATGAM. Because these reactions are reported voluntarily from a population of uncertain size, it is not always possible to reliably estimate their frequency or establish a causal relationship to drug exposure.

Infections and infestations: Sepsis, Hepatitis viral, Localized infection, Systemic infection (bacterial, viral, fungal).

Blood and lymphatic system disorders: Anemia, Eosinophilia, Granulocytopenia, Hemolysis, Hemolytic anemia, Neutropenia, Pancytopenia

Psychiatric disorders: Confusional state, Disorientation

Nervous system disorders: Dyskinesia, Syncope, Tremor

Cardiac disorders: Cardiac failure congestive

Vascular disorders: Deep vein thrombosis, Vasculitis

Respiratory, thoracic and mediastinal disorders: Apnea, Cough, Epistaxis, Oropharyngeal pain

Gastrointestinal disorders: Abdominal pain, Gastrointestinal hemorrhage, Gastrointestinal perforation, Oral pain

Skin and subcutaneous tissue disorders: Hyperhidrosis

Musculoskeletal and connective tissue disorders: Flank pain, Muscle rigidity, Myalgia, Pain in extremity

Renal and urinary disorders: Kidney enlargement, Kidney rupture, Renal failure acute

Congenital, familial and genetic disorders: Aplasia

General disorders and administration site conditions: Infusion site erythema, Infusion site swelling, Pain

7 DRUG INTERACTIONS

A potential pharmacodynamic interaction concerns the concomitant administration of ATGAM with corticosteroids and other immunosuppressants, which are associated with an increased susceptibility to bacterial, viral and fungal infections, as they inhibit the immune system. The severity of the infections such as septicemia may be masked and their clinical presentations may be atypical.

Monitor patients receiving ATGAM and immunosuppressive agents such as corticosteroids when the dose of corticosteroids and other immunosuppressants is being reduced, since this adjustment of dose may result in reduced immunosuppression and lead to development of previously masked reactions to ATGAM.

8 USE IN SPECIFIC POPULATIONS

8.1 Pregnancy

Risk Summary

There are no adequate and well-controlled studies in pregnant women. There is a limited amount of data from the use of ATGAM in pregnant women. It is also not known whether ATGAM can cause fetal harm when administered to a pregnant woman or can affect reproduction capacity. The outcome of pregnancies cannot be determined. Use ATGAM during pregnancy only if the potential benefit to the mother justifies the potential risk to the fetus.

The estimated background risk of major birth defects and miscarriage for the indicated population is unknown. All pregnancies have a background risk of birth defect, loss, or other adverse outcome. In the U.S. general population, the estimated background risk of major birth defects and miscarriage in clinically recognized pregnancies is 2% to 4% and 15% to 20%, respectively.

Data

In embryo-fetal toxicity studies, ATGAM was administered to rats and cynomolgus monkeys for 11 and 16 days, respectively during organogenesis. In rats, hypoplastic cervical vertebrae, a finding consistent with delayed skeletal development, were observed in fetuses whose dams received ATGAM at doses of 100 mg/kg/day during organogenesis. In monkey reproduction studies, maternal toxicity (vaginal bleeding, decreased body weight and loss of appetite) was observed with ATGAM doses ≥20 mg/kg/day after 16 days of dosing. Fetal deaths occurred in dams treated with 20 mg/kg/day ATGAM earlier in organogenesis (days 20‑35), but not when treatment was given at a later part of organogenesis (days 35-50). The maternal and fetal deaths were attributed to maternal anemia due to red blood cell antigen that humans do not share. Therefore, this toxicity is not considered relevant to human fetal development.

8.2 Lactation

Risk Summary

It is not known if ATGAM is excreted in human milk. Because many drugs are excreted in human milk and because of the potential for serious adverse reactions in breast-feeding neonates and infants from ATGAM, a decision should be made whether to discontinue breast-feeding or to discontinue the drug taking into account the importance of the drug to the mother.

Data

In animal studies, a single dose of ATGAM up to 40 mg/kg was not detected at the limit of quantification in the milk of lactating cynomolgus monkeys.

8.3 Females and Males of Reproductive Potential

Contraception

Females

It is not known if ATGAM can cause fetal harm when administered to a pregnant woman [see Use in Specific Populations (8.1)]. Advise females of reproductive potential to use effective contraception during treatment with ATGAM and for at least 10 weeks after cessation of therapy.

Males

Advise males with a female partner of reproductive potential to use effective contraception during treatment with ATGAM and for at least 10 weeks after cessation of therapy.

Infertility

In fertility studies, ATGAM at doses 10, 20 and 40 mg/kg/day was administered to cynomolgus monkeys (Macaca fascicularis) for 14 days either before (male monkeys) or before and after (female monkeys) cohabitation with untreated mates. ATGAM treatment was not associated with male or female hormonal or copulation behavior changes. A decrease in fertility index in female monkeys receiving ATGAM was seen. Female toxicity, including death, was observed with ATGAM doses of ≥20 mg/kg/day. While the etiology of this toxicity is uncertain, it may be attributed to hemolytic anemia due to cross-reactivity of ATGAM to a monkey red blood antigen.

8.4 Pediatric Use

Experience with children has been limited. ATGAM has been administered safely to a small number of pediatric renal allograft recipients and pediatric aplastic anemia patients at dosage levels comparable to those in adults.

8.5 Geriatric Use

Clinical experience in a limited number of elderly patients (≥65 years of age) has not identified differences in responses between the elderly and younger patients. Select the dose for an elderly patient with caution, starting at the low end of the dosage range, reflecting the greater frequency of decreased hepatic, renal, or cardiac function, and of comorbidities or other drug therapy in this age group.

10 OVERDOSAGE

The maximum tolerated dose of ATGAM Sterile Solution is expected to vary from patient to patient due to the biological nature of the product. The largest single daily dose known to be administered to one patient (renal allograft recipient) was 7,000 mg administered at a concentration of approximately 10 mg/mL Sodium Chloride Injection, USP, seven times the recommended total dose and infusion concentration. In this patient, the administration of ATGAM was not associated with any signs of acute intoxication or late sequelae.

A maximum therapeutic dose has not been established therefore the definition of overdose for ATGAM has not been clearly defined. Some renal allograft patients have received up to 50 doses in 4 months, and others have received 28-day courses of 21 doses followed by as many as 3 more courses for the treatment of acute rejection. The incidence of toxicologic manifestations did not increase with any of these regimens; however, close monitoring of the patient is recommended.

11 DESCRIPTION

ATGAM Sterile Solution contains lymphocyte immune globulin, anti-thymocyte globulin [equine]. It is the purified, concentrated, and sterile gamma globulin, primarily monomeric IgG, from hyperimmune serum of horses immunized with human thymus lymphocytes. ATGAM is a transparent to slightly opalescent aqueous protein solution. It may appear colorless to faintly pink or faintly brown and is nearly odorless. It may develop a slight granular or flaky deposit [see Dosage and Administration (2.2)].

Precise methods of determining the potency of ATGAM have not been established, thus activity may potentially vary from lot to lot. Before release for clinical use, each lot of ATGAM is tested to assure its ability to inhibit rosette formation between human peripheral lymphocytes and sheep red blood cells in vitro. In each lot, antibody activity against human red blood cells and platelets is also measured and determined to be within acceptable limits. Only lots that meet the acceptance criteria for pyrogens and test negative for antihuman serum protein antibody and antiglomerular basement membrane antibody are released.

Each milliliter of ATGAM contains 50 mg of horse gamma globulin stabilized in 0.3 molar glycine to a pH of approximately 6.8.

12 CLINICAL PHARMACOLOGY

12.1 Mechanism of Action

ATGAM is composed of antibodies that bind a wide variety of proteins on the surface of lymphocytes. In addition, ATGAM binds to granulocytes, platelets, bone marrow cells, and other cell types. The mechanism of ATGAM-induced immunosuppression has not been determined. Published data indicate that the primary mechanism is the depletion of circulating lymphocytes, with greatest effect on T lymphocytes. Lymphocyte depletion may be caused by complement dependent lysis and/or activation-induced apoptosis. In addition, immunosuppression may be mediated by the binding of antibodies to lymphocytes which results in partial activation and induction of T lymphocyte anergy.

The mechanism of ATGAM therapy for aplastic anemia is attributed to its immunosuppressive actions. In addition, ATGAM directly stimulates the growth of hematopoietic stem cells and release of hematopoietic growth factors such as interleukin-3 and granulocyte/macrophage colony stimulating factor.

12.2 Pharmacodynamics

Standard pharmacodynamic studies were not performed. Key efficacy endpoints in the ATGAM pivotal studies were clinical responses rather than pharmacodynamic endpoints [see Clinical Studies (14)].

12.3 Pharmacokinetics

Distribution

In a multicenter study, ATGAM pharmacokinetics were evaluated in 27 renal transplant patients. During infusion of 10 to 15 mg/kg/day, the mean peak value was found to be 727 ± 310 μg/mL.

Metabolism and Elimination

The half-life of equine immunoglobulin after ATGAM infusion was found to be 5.7 ± 3.0 days in renal transplant patients (n=27). The range for half-life was 1.5 to 13 days.

Specific Populations

Ethnicity

ATGAM pharmacokinetics were evaluated in a study of 6 Japanese adult patients with moderate or severe aplastic anemia. When administered via intravenous infusion at a dose of 10 mg/kg/day (n=3) or 20 mg/kg/day (n=3) for 8 days, the mean concentration was 1,180 ± 240 µg/mL and 2,060 ± 340 µg/mL, respectively at 1 hour after completion of infusion on Day 8. The apparent elimination half-life after the last dose varied from 1.3 to 6 days in these patients.

13 NONCLINICAL TOXICOLOGY

13.1 Carcinogenesis and Mutagenesis

Carcinogenicity and pre-/post-natal development studies have not been conducted on ATGAM.

14 CLINICAL STUDIES

14.1 Renal Allograft Rejection

US Studies

The effectiveness of ATGAM for treatment of acute allograft rejection was evaluated in three different treatment applications: as a substitute for standard therapy, in conjunction with standard therapy at the time of diagnosis of the first rejection episode, and in conjunction with standard therapy in steroid resistant rejection episodes.

A randomized controlled trial of the use of ATGAM as a substitute for standard therapy for treatment of the first acute rejection episode was conducted at one transplant center in recipients of living related renal allografts. A total of 22 patients were studied; 11 in each of the two treatment groups [ATGAM versus standard therapy (bolus doses of Solu-Medrol®)]. Patients randomized to the ATGAM group received 14–21 doses of ATGAM therapy, starting on the day the rejection was diagnosed. ATGAM was administered daily according to a dose-by-rosette regimen which resulted in a mean daily dose of approximately 15 mg/kg. Patients randomized to the control group received Solu-Medrol® at a dosage of 15 mg/kg starting on the day the rejection was diagnosed, administered either daily or on alternate days for 3 to 7 doses to complete a maximum total dose of 5,000 mg for the course of the rejection episode. In this study, ATGAM was at least effective as standard therapy for treatment of acute allograft rejection. All 11 ATGAM‑treated patients achieved resolution of first rejection compared with 10/11 control patients. At one year, the functional graft survival rate was 91% in the ATGAM group (10/11) and 64% in the control group (7/11). Patient survival was similar in the two treatment groups (11/11 ATGAM patients versus 10/11 control patients).

The effect of ATGAM when administered in conjunction with standard therapy at the time of diagnosis of the first rejection episode was studied under two different protocols with cadaveric and living related renal allograft rejection patients. The results from these studies demonstrate the efficacy associated with the addition of ATGAM to standard therapy for treatment of the first rejection episode in renal allograft recipients. In Study 1, a randomized controlled, two center trial of ATGAM use for treatment of acute rejection in cadaveric renal allograft rejection patients, the addition of ATGAM to standard rejection therapy (methylprednisolone sodium succinate) resulted in an increased frequency of resolution of the first acute rejection episode which was statistically significant (p <0.01). ATGAM-treated patients achieved a rejection resolution rate of 80% (36/45) compared with 54% (25/46) in the control group. There was a statistically significant improvement in functional graft survival favoring the ATGAM group (p <0.01), and a statistically significant steroid sparing effect during the first rejection episode among patients in the ATGAM group. There was no difference in the patient survival rate between the two treatment groups. Study 2 was a randomized controlled trial conducted at five different transplant centers. In this study, the addition of ATGAM to standard rejection therapy (bolus doses of Solu-Medrol®) for treatment of acute rejection in recipients of living related renal transplants resulted in an increased frequency of rejection resolution and improvement in functional graft survival. Due to the small sample size, the difference between the ATGAM group and the control group in functional graft survival rate did not achieve statistical significance. Marginal statistical significance was demonstrated in rejection reversal rate and intravenous steroid sparing among ATGAM patients (p=0.10 and p=0.07). Patient survival rates were similar in the two treatment groups.

Results from randomized controlled trials in patients with first acute renal allograft rejection episodes refractory to conventional steroid therapy have demonstrated that ATGAM, when administered in conjunction with standard therapy, yields efficacy results superior to those of standard therapy alone. One study investigated two different regimens of ATGAM; immediate and delayed therapy. Patients were enrolled at the time of first rejection episode and randomized among three treatment groups: control (no ATGAM), immediate ATGAM, and delayed ATGAM. Patients in all three treatment groups received standard rejection therapy in the form of bolus doses of Solu-Medrol® 15 mg/kg/day IV, while patients in the two ATGAM groups received ATGAM therapy in addition to Solu-Medrol®. In the immediate ATGAM group, ATGAM administration started at the time of diagnosis of rejection (concurrent with standard therapy). In the delayed ATGAM group, ATGAM administration started on rejection day 4 (following the first three doses of Solu-Medrol®). Patients in both of the treated groups received from 10 to 21 doses of ATGAM. Results favored the two ATGAM groups (and particularly the immediate ATGAM group) in both outcome of first rejection and functional graft survival. The improvement in functional graft survival was statistically significant (p=0.05). There was also a statistically significant difference in patient survival rate favoring the ATGAM-treated groups (p=0.02).

The effectiveness of ATGAM for reversal of acute renal allograft rejection was also demonstrated in other controlled studies performed in various medical centers. In these studies, ATGAM was administered at time of diagnosis of the first rejection episode at a range of 10 to 15 mg/kg per day for 14 to 15 days, followed by alternate‑day therapy for a total of 21 doses in 28 days.

14.2 Aplastic Anemia

The use of ATGAM for the treatment of moderate to severe aplastic anemia in patients unsuitable for bone marrow transplantation is based on data from three controlled studies.

The effectiveness of the ATGAM therapy in the studies described below was evaluated by the hematological response and survival rates (Table 3).

10 to 20 mg/kg daily for 8 to 14 days

Study 1

A total of 41 patients with moderate or severe aplastic anemia ages 6 to 69 years, who were not candidates for bone marrow transplantation were enrolled in a randomized controlled study. The objective of this study was to determine the efficacy of ATGAM as a single agent, in restoring hematopoiesis in patients with moderate to severe aplastic anemia. Twenty-one (n = 21) patients in the ATGAM treatment group received 20 mg/kg/day for 8 days, while control patients (n = 20) were observed for 3 months. All patients were given oral prednisone (40 mg/m^2/day) starting on day 8 then tapered over 1 to 2 weeks.

At 3 months post-study enrollment, 11 patients in the supportive care group who showed no improvement became eligible and were crossed over to receive ATGAM therapy. Efficacy was evaluated as sustained improvement in peripheral blood counts within 3 months of entry into the study. A statistically significant (p<0.01) difference was observed between the two treatment groups in hematological improvement based on the investigator's evaluation; 11 of 21 (52%) patients in the ATGAM group responded, compared with no patients (0 of 20) in the control group. Six of the 11 crossover patients from the control group showed improvement after 3 months of therapy. Overall, of 32 patients in both the ATGAM group and the control group who crossed over to receive ATGAM, 17 patients (53%) had a hematological improvement. Estimated 1-year survival rate was 62% for all 32 patients treated with ATGAM. The 2-year survival rate was 100% among the ATGAM responders [17 of the 32 patients (53%) compared to 14% for the nonresponders].

Fever, chills, and erythematous or urticarial rash were seen in all ATGAM treated patients. Platelet counts decreased during ATGAM infusion and daily platelet transfusions were necessary. Serum sickness occurred in all patients within 6 to 18 days of ATGAM initiation and was well-controlled with standard therapy. Three patients experienced transient hypotension.

Study 2

A randomized double-blind, placebo prospective, controlled study was conducted to compare the safety and efficacy of ATGAM and androgen (oxymetholone; OXY) immunosuppressive therapy with the combination of ATGAM, androgen (OXY) and an infusion of human leukocyte antigen (HLA) mismatched bone marrow in patients with severe aplastic anemia who were not candidates for bone marrow transplantation. Allocation to treatment group was based on the availability of mismatched bone marrow donors. A total of 42 patients, ages 1 to 69 years were treated. Eighteen patients received ATGAM at a dose of 16 mg/kg/day for 10 doses with concomitant androgens (OXY) at a dose of 3 mg/kg/day for a minimum of 3 months, and 24 patients received an infusion of bone marrow from an HLA mismatched donor 48 hours after the completion of ATGAM treatment.

At 3 months after entry into the study, 51% of patients with disease of idiopathic etiology (21 of the 41 evaluable patients from both groups) showed improvement based on investigator's evaluation of transfusion requirements and peripheral blood counts. Hematological response rate (complete/moderate based on sponsor's evaluation) at 3 months for the ATGAM and androgen group was 44% compared with 43% for the group receiving ATGAM, androgen and bone marrow infusion. The group of patients who received mismatched bone marrow infusion had better estimated 1-year survival rate, although the difference between these estimates was not statistically significant (p=0.14); 83% at 12 months for the group receiving bone marrow infusion versus 59% for the ATGAM and androgen alone group. Estimated 1-year survival rate for both groups combined was 73%.

The most commonly reported adverse events were rash, fever, arthralgias, chills, headache, myalgia and pruritus.

A pooled analysis of data from Studies 1 and 2 revealed an overall estimated 1-year survival rate of 69% in ATGAM-treated patients.

Study 3

A total of 53 patients (3 to 76 years of age) participated in this randomized, placebo-controlled, double-blind study to determine if androgens add to the efficacy of ATGAM in providing favorable hematologic response rates in patients with moderate to severe aplastic anemia. All patients were treated with ATGAM 20 mg/kg/day IV for 8 days, and were randomized to receive the oral androgen (oxymetholone 4 mg/kg/day or fluoxymesterone 25 mg/m^2/day) (n = 26), or a matched placebo (n = 27). Both groups received oral prednisone (40 mg/m^2/day) beginning on day 8 which was tapered and discontinued in 1 to 2 weeks. A group of historical controls from previous studies (n = 68; 1 to 72 years of age) who received ATGAM (20 mg/kg/day IV for 8 days) without androgens were included for treatment results comparison. The proportions of subjects who presented complete or partial response at 6 months were 42% in the ATGAM plus androgen group, 44% in the ATGAM plus placebo group, and 51% in the historical controls. The difference in response rates was not significant (p>0.9). Survival at 2 years was also comparable in the two groups for patients with severe aplastic anemia; 55% in the ATGAM plus androgen group compared with 50% in the ATGAM plus placebo group (p=0.65), and 56% for the historical controls. In patients with moderate aplastic anemia, two-year survival for the ATGAM plus androgen group was 63% compared with 100% in those receiving ATGAM plus placebo and 72% in the historical controls who received ATGAM alone.

Adverse reactions in both groups were comparable and included rash, chills, gastrointestinal disturbances, and joint pain during ATGAM infusion, as well as symptoms of serum sickness in all patients. Five patients had asymptomatic sinus bradycardia; six patients required antihypertensive therapy. Alanine transaminase or alkaline phosphatase levels increased to >2 times the upper limits of normal in 7 patients receiving ATGAM plus androgen, and in nine patients receiving ATGAM plus placebo.

Table 3. Key Studies with ATGAM for the Treatment of Aplastic Anemia (10 to 20 mg/kg/day for 8 to 14 days)
Study | ATGAM + comparator or other therapy | No. of subjects | Response rate % (endpoint) [Hematologic response was defined differently in different studies.] | P Value | Survival rate % (time point) | P Value (or 95% CI)
Study 1 | ATGAM | 21 | 47 [Sponsor's evaluation of response] / 52 [Investigator's evaluation of response] (3 mo) | <0.01/<0.01 | 62 [This survival estimate includes the 21 subjects who were randomized to receive ATGAM, plus another 11 subjects who were crossed over from the control group.] (12 mo) | NA
Study 1 | Control | 20 | 6/ 0 (3 mo) | <0.01/<0.01 | 62 (12 mo) | NA
Study 2 | ATGAM + Bone marrow infusion | 24 | 43 (3 mo) | Not reported | 83 (12 mo) | =0.14
Study 2 | ATGAM | 18 | 44 (3 mo) | Not reported | 59 (12 mo) | =0.14
Study 3 | ATGAM + Androgen | 26 | 42 (6 mo) | >0.9 | 55 [Patients with severe aplastic anemia only.] (24 mo) | =0.65
Study 3 | ATGAM + Placebo | 27 | 44 (6 mo) | >0.9 | 50 (24 mo) | =0.65
Study 3 | ATGAM historical controls | 68 | 51 (6 mo) | NA | 56 (24 mo) | -

15 REFERENCES

1. Hardy MA, Nowygrod R, Elberg A, Appel G. Use of ATG in treatment of steroid-resistant rejection. Transplantation 1980; 29(2):162–4.
2. Nowygrod R, Appel G, Hardy MA. Use of ATG for reversal of acute allograft rejection. Transplant Proc 1981; 13(1):469–72.
3. Filo RS, Smith EJ, Leapman SB. Reversal of acute renal allograft rejection with adjunctive ATG therapy. Transplant Proc 1981; 13(1):482–90.
4. Shield CF III, Cosimi AB, Tolkoff Rubin N, et al. Use of antithymocyte globulin for reversal of acute allograft rejection. Transplantation 1979; 28(6):461–4.
5. Rubin RH, Cosimi AB, Hirsch MS, Herrin JT. Effects of antithymocyte globulin on cytomegalovirus infection in renal transplant recipients. Transplantation 1981; 31(2):143–5.
6. Cosimi AB, Wortis HH, Delmonico FL, Russell PS. Randomized clinical trial of antithymocyte globulin in cadaver renal allograft recipients: importance of T cell monitoring. Surgery 1976; 80(2):155–63.
7. Wechter WJ, Brodie JA, Morrell RM, et al. Antithymocyte globulin (ATGAM) in renal allograft recipients: multicenter trials using a 14-dose regimen. Transplantation 1979; 28(4):294–302.
8. Butt KMH, Zielinski CM, Parsa I, et al. Trends in immunosuppression for kidney transplantation. Kidney Int 1978; 13(Suppl 8): S95–S8.
9. Ettenger RB, Rosenthal JT, Marik JL, et al. Improved cadaveric renal transplant outcome in children. Pediatric Nephrol 1991; 5:137–42.

16 HOW SUPPLIED/STORAGE AND HANDLING

ATGAM Sterile Solution, containing 50 mg/mL lymphocyte immune globulin, anti-thymocyte globulin [equine], is supplied as follows:

5 – 5 mL ampoules: NDC 0009-7224-02

STORAGE AND HANDLING

Store in a refrigerator at 2° to 8°C (36° to 46°F). DO NOT FREEZE. Store in the original carton to protect from light.

For storage conditions of diluted solution, see Dosage and Administration (2.2).

17 PATIENT COUNSELING INFORMATION

Advise patients receiving ATGAM that they will be monitored in a facility equipped and staffed with adequate laboratory and supportive medical resources.

Anaphylaxis

Advise the patient that ATGAM may be discontinued and immediate medical attention will be provided if any signs/symptoms of anaphylaxis occur [see Warnings and Precautions (5.1)].

Cytokine Release Syndrome

Advise the patient on the risk of cytokine release syndrome [see Warnings and Precautions (5.2)].

Infusion-Associated Reactions

Advise the patient on the clinical signs associated with infusion-associated reactions [see Warnings and Precautions (5.3)].

Serum Sickness

Advise the patient on the clinical signs associated with serum sickness [see Warnings and Precautions (5.4)].

Transmissible Infectious Agents

Despite screening and testing, products manufactured using components of human blood such as ATGAM may carry a risk of transmitting infectious agents (e.g., viruses). Discuss the risks and benefits of therapy with patients before initiating treatment [see Warnings and Precautions (5.5)].

Infections

Advise the patient to report any signs and symptoms of infection (e.g., fever, sweating, chills, muscle aches, cough, shortness of breath, diarrhea, or stomach pain) [see Warnings and Precautions (5.6)].

Thrombocytopenia and Neutropenia

Advise the patient to report any signs and symptoms of thrombocytopenia and/or neutropenia (e.g., unusual bleeding, bruising, rash of dark red spots under the skin, fever, sweating, chills, muscle aches, cough, shortness of breath, diarrhea, or stomach pain) [see Warnings and Precautions (5.8)].

Hepatic and Renal Function Tests

Advise the patient that monitoring of liver and renal function will occur. Advise the patient of abnormal liver and renal function test results [see Warnings and Precautions (5.9)].

Healthcare providers should refer to labels.fda.gov or DailyMed for the most updated version of the labeling.

This product's labeling may have been updated. For the most current prescribing information, please visit www.pfizer.com. For medical information about ATGAM, please visit www.pfizermedinfo.com or call 1-800-438-1985.

U.S. Govt. License No. 1216

LAB-0019-13.0

PRINCIPAL DISPLAY PANEL - 5 mL Ampule Label

NDC 0009-7224-01

5 mL

Atgam®

lymphocyte immune globulin,
anti-thymocyte globulin (equine)

250 mg protein

50 mg/mL For Intravenous use only

DOSAGE AND USE: See accompanying
prescribing information. Protect from light.

ATTENTION—May contain particles; this is normal.
Use 0.2 micron to 1.0 micron in-line filter. See insert.

Manufactured by
Pharmacia & Upjohn Company LLC
A subsidiary of Pfizer Inc.
New York, NY 10001

U.S. Govt. License No. 1216
Rx only

PAA210475

LOT / EXP

PRINCIPAL DISPLAY PANEL - 5 mL Ampule Carton

NDC 0009-7224-02
Contains 5 of NDC 0009-7224-01

5–5 mL Ampoules
(single use containers)

Atgam®

lymphocyte immune globulin,
anti-thymocyte globulin (equine)

250 mg protein

50 mg/mL

ATTENTION—This product may contain a granular
or flaky deposit; this is normal. See infusion
instructions described in the enclosed product insert.

Sterile Solution For Intravenous Use Only

Pfizer Hospital
Rx only